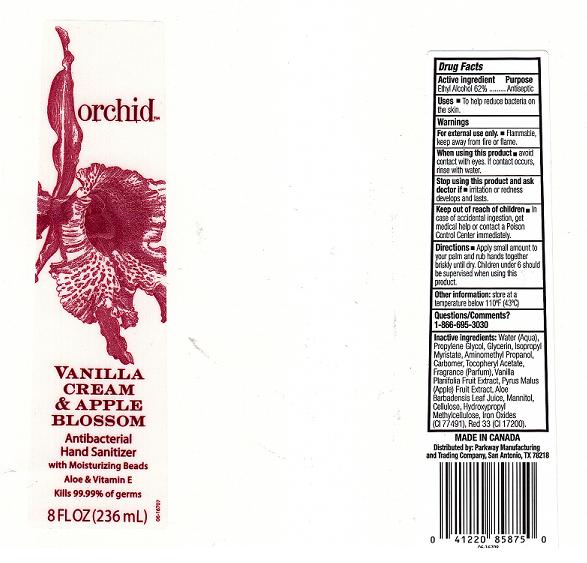 DRUG LABEL: VANILLA CREAM AND APPLE BLOSSOM ANTIBACTERIAL HAND SANITIZER
NDC: 37808-265 | Form: GEL
Manufacturer: HEB
Category: otc | Type: HUMAN OTC DRUG LABEL
Date: 20110103

ACTIVE INGREDIENTS: ALCOHOL 62 mL/100 mL
INACTIVE INGREDIENTS: WATER; PROPYLENE GLYCOL; GLYCERIN; ISOPROPYL MYRISTATE; AMINOMETHYLPROPANOL; CARBOMER 934; .ALPHA.-TOCOPHEROL ACETATE, D-; VANILLA; APPLE; ALOE VERA LEAF; MANNITOL; POWDERED CELLULOSE; HYPROMELLOSES; FERRIC OXIDE RED; D&C RED NO. 33

DRUG FACTS

ACTIVE INGREDIENT

ETHYL ALCOHOL 62 PERCENT

PURPOSE

ANTISEPTIC

USES

TO HELP REDUCE BACTERIA ON THE SKIN.

WARNINGS

FOR EXTERNAL USE ONLY. FLAMMABLE, KEEP AWAY FROM FIRE OR FLAME.

WHEN USING THIS PRODUCT

AVOID CONTACT WITH EYES.IF CONTACT OCCURS, RINSE WITH WATER.

STOP USING THIS PRODUCT AND ASK DOCTOR IF

IRRITATION OR REDNESS DEVELOPS AND LASTS.

KEEP OUT OF REACH OF CHILDREN

IN CASE OF ACCIDENTAL INGESTION, GET MEDICAL HELP OR CONTACT A POISON CONTROL CENTER IMMEDIATELY.

DIRECTIONS

APPLY SMALL AMOUNT TO YOUR PALM AND RUB HANDS TOGETHER BRISKLY UNTIL DRY. CHILDREN UNDER 6 SHOULD BE SUPERVISED WHEN USING THIS PRODUCT.

OTHER INFORMATION

STORE AT A TEMPERATURE BELOW 110^0F (43^0C).

QUESTIONS OR COMMENTS

1-866-695-3030

INACTIVE INGREDIENTS

WATER, PROPYLENE GLYCOL, GLYCERIN, ISOPROPYL MYRISTATE, AMINOMETHYL PROPANOL, CARBOMER, TOCOPHERYL ACETATE, FRAGRANCE, VANILLA PLANIFOLIA FRUIT EXTRACT, PYRUS MALUS (APPLE) FRUIT EXTRACT, ALOE BARBADENSIS LEAF JUICE, MANNITOL, CELLULOSE, HYDROXYPROPYL METHYLCELLULOSE, IRON OXIDES (CI 77491), RED 33 (CI 17200).